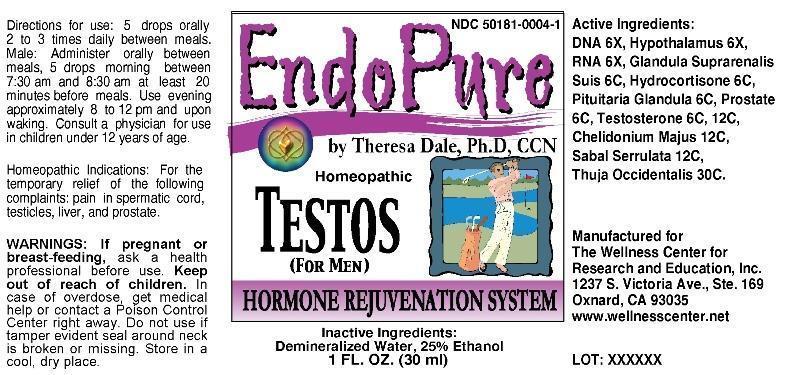 DRUG LABEL: Endopure Testos for Men
NDC: 50181-0004 | Form: LIQUID
Manufacturer: The Wellness Center for Research and Education, Inc.
Category: homeopathic | Type: HUMAN OTC DRUG LABEL
Date: 20250530
DEA Schedule: CIII

ACTIVE INGREDIENTS: HERRING SPERM DNA 6 [hp_X]/1 mL; SUS SCROFA HYPOTHALAMUS 6 [hp_X]/1 mL; SACCHAROMYCES CEREVISIAE RNA 6 [hp_X]/1 mL; HYDROCORTISONE 6 [hp_C]/1 mL; SUS SCROFA ADRENAL GLAND 6 [hp_C]/1 mL; SUS SCROFA PITUITARY GLAND, POSTERIOR 6 [hp_C]/1 mL; SUS SCROFA PROSTATE 6 [hp_C]/1 mL; TESTOSTERONE 6 [hp_C]/1 mL; CHELIDONIUM MAJUS 12 [hp_C]/1 mL; SAW PALMETTO 12 [hp_C]/1 mL; THUJA OCCIDENTALIS LEAFY TWIG 30 [hp_C]/1 mL
INACTIVE INGREDIENTS: WATER; ALCOHOL

Drug Facts:

ACTIVE INGREDIENTS:

DNA 6X, Hypothalamus (suis) 6X, RNA 6X, Glandula suprarenalis suis 6C, Hydrocortisone 6C, Pituitaria glandula 6C, Prostate (suis) 6C, Testosterone 6C, 12C, Chelidonium majus 12C, Sabal serrulata 12C, Thuja occidentalis 30C.

HOMEOPATHIC INDICATIONS:

For the temporary relief of the following complaints: pain in spermatic cord, testicles, liver, and prostate.

WARNINGS:

If pregnant or breast-feeding, ask a health professional before use.

Keep out of reach of children. In case of overdose, get medical help or contact a Poison Control Center right away.

Do not use if tamper evident seal around neck is broken or missing.

Store in a cool, dry place.

DIRECTIONS FOR USE:

5 drops orally 2 to 3 times daily between meals. Male: Administer orally between meals, 5 drops morning between 7:30 am and 8:30 am at least 20 minutes before meals. Use evening approximately 8 to 12 pm and upon waking. Consult a physician for use in children under 12 years of age.

INACTIVE INGREDIENTS:

Demineralized water, 25% Ethanol.

Keep out of reach of children. In case of overdose, get medical help or contact a Poison Control Center right away.

HOMEOPATHIC INDICATIONS:

For the temporary relief of the following complaints: pain in spermatic cord, testicles, liver, and prostate.

QUESTIONS:

Manufactured for

The Wellness Center for

Research and Education, Inc.

1237 S. Victoria Ave., Ste. 169

Oxnard, CA 93035

www.wellnesscenter.net

Package Label Display

NDC 50181-0004-1

EndoPure

by Theresa Dale, Ph.D, CCN

Homeopathic

TESTOS For Men

HORMONE REJUVENATION SYSTEM

1 FL. OZ. (30 ml)